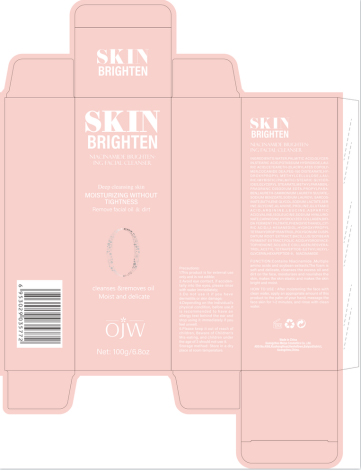 DRUG LABEL: Cleanser
NDC: 84673-012 | Form: EMULSION
Manufacturer: Guangzhou Meiya Cosmetics Co. ,Ltd.
Category: otc | Type: HUMAN OTC DRUG LABEL
Date: 20241002

ACTIVE INGREDIENTS: NIACINAMIDE 100 mg/1 g
INACTIVE INGREDIENTS: WATER 46.769 mg/1 g; STEARIC ACID 9.2 mg/1 g; PALMITIC ACID 13.8 mg/1 g; LAURETH-7 0.07 mg/1 g; CETEARETH-25 1 mg/1 g; PEG-150 DISTEARATE 0.4925 mg/1 g; METHYLPARABEN 0.2 mg/1 g; PROPYLPARABEN 0.1 mg/1 g; SODIUM LACTATE 0.0005 mg/1 g; GLYCINE 0.0004 mg/1 g; ALANINE 0.0003 mg/1 g; PROLINE 0.00025 mg/1 g; ISOLEUCINE 0.00025 mg/1 g; ASPARTIC ACID 0.00025 mg/1 g; VALINE 0.00025 mg/1 g; SODIUM LAUROYL SARCOSINATE 0.003 mg/1 g; PHENOXYETHANOL 0.00003 mg/1 g; FOLIC ACID 0.000002 mg/1 g; 1,2-HEXANEDIOL 0.000002 mg/1 g; HYDROXYPROPYL TETRAHYDROPYRANTRIOL 0.000005 mg/1 g; HEXAPEPTIDE-9 0.00000002 mg/1 g; ACETYL TETRAPEPTIDE-5 0.0000001 mg/1 g; ETHYLHEXYLGLYCERIN 0.00000004 mg/1 g; RESVERATROL 0.0000003 mg/1 g; SERINE 0.00045 mg/1 g; HYDROXYACETOPHENONE 0.0000005 mg/1 g; POTASSIUM HYDROXIDE 5.75 mg/1 g; LAURIC ACID 4 mg/1 g; SODIUM BENZOATE 0.0175 mg/1 g; BUTYLENE GLYCOL 0.002 mg/1 g; ARGININE 0.00025 mg/1 g; LEUCINE 0.00025 mg/1 g; CARNOSINE 0.0001 mg/1 g; GLYCERIN 10 mg/1 g

PURPOSE

Function:Contains Niacinamide ,Multiple amino acids and soybean extracts.The foam is soft and delicate, cleanses the excess oil and dirt on the face, moisturizes and nourishes the skin, makes the skin elastic and makes the skin bright and moist.

INDICATIONS AND USAGE

HOW TO USE : After moistening the face with clean water, apply an appropriate amount of this product to the palm of your hand, massage the face skin for 1-2 minutes, and rinse with clean water.

WARNINGS

1. This product is for external use only and is not edible;

2. Avoid eye contact, if accidentally into the eyes, please rinse with water immediately;

3. Do not use it if you have dermatitis or skin damage;

4. Depending on the individual's physical condition, before use,It is recommended to have an allergy test behind the ear and stop using it immediately if you feel unwell.

5. Please keep it out of reach of children, Beware of Children's Mis-eating, and children under the age of 3 should not use it.

STOP USE

1. Avoid eye contact, if accidentally into the eyes, please rinse with water immediately;

2. Do not use it if you have dermatitis or skin damage;

3. Depending on the individual's physical condition, before use,It is recommended to have an allergy test behind the ear and stop using it immediately if you feel unwell.

DO NOT USE

1. Avoid eye contact, if accidentally into the eyes, please rinse with water immediately;

2. Do not use it if you have dermatitis or skin damage;

3. Depending on the individual's physical condition, before use,It is recommended to have an allergy test behind the ear and stop using it immediately if you feel unwell.

KEEP OUT OF REACH OF CHILDREN

Please keep it out of reach of children, Beware of Children's Mis-eating, and children under the age of 3 should not use it.

WHEN USING

1. This product is for external use only and is not edible;

2. Avoid eye contact, if accidentally into the eyes, please rinse with water immediately;

3. Do not use it if you have dermatitis or skin damage;

4. Depending on the individual's physical condition, before use,It is recommended to have an allergy test behind the ear and stop using it immediately if you feel unwell.

5. Please keep it out of reach of children, Beware of Children's Mis-eating, and children under the age of 3 should not use it.